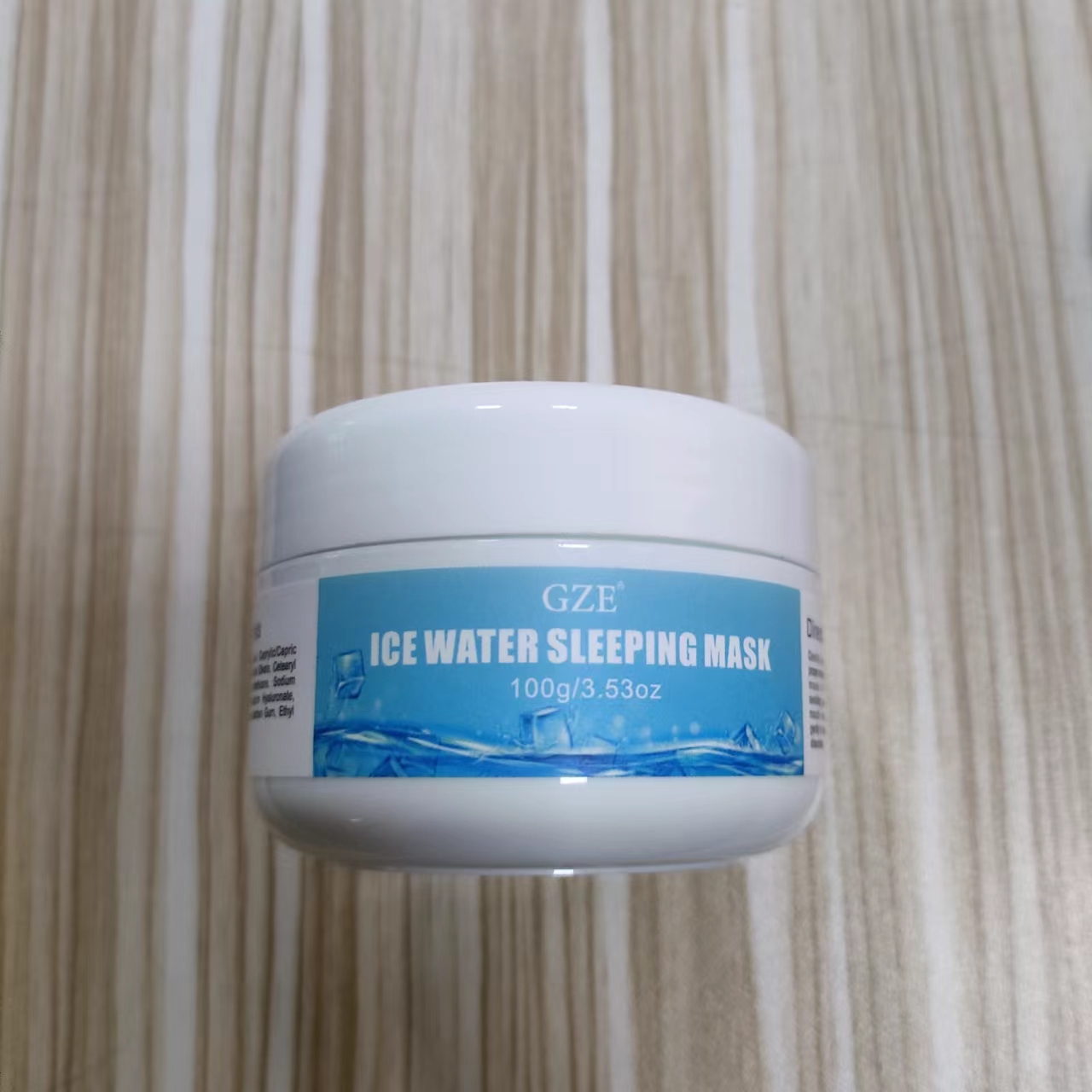 DRUG LABEL: GZE ICE WATER SLEEPING MASK
NDC: 74458-089 | Form: CREAM
Manufacturer: Guangzhou Yilong Cosmetics Co., Ltd
Category: otc | Type: HUMAN OTC DRUG LABEL
Date: 20241129

ACTIVE INGREDIENTS: ARGININE 1 g/100 g; ALLANTOIN 1 g/100 g
INACTIVE INGREDIENTS: CETEARYL OLIVATE; DIMETHICONE; ADENOSINE; SORBITAN OLIVATE; CETEARYL ALCOHOL; CARBOMER; SODIUM POLYACRYLATE (8000 MW); XANTHAN GUM; PANTHENOL; SNAIL SECRETION FILTRATE; SODIUM HYALURONATE; STEARIC ACID; CAPRYLIC/CAPRIC TRIGLYCERIDE; PHENOXYETHANOL; BETAINE; ETHYL HEXANEDIOL

GZE ICE WATER SLEEPING MASK

ACTIVE INGREDIENT

Arginine 1%
Allantoin 1%

INACTIVE INGREDIENT

Snail Secretion Filtrate

Betaine

Caprylic/Capric Triglyceride

Cetearyl Olivate

Sorbitan Olivate

Cetearyl Alcohol

Carbomer

Dimethicone

Sodium Polyacrylate

Phenoxyethanol

Sodium Hyaluronate

Stearic Acid

Panthenol

Xanthan Gum

Ethyl Hexanediol

Adenosine

INDICATIONS AND USAGE

Apply before bedtime by rubbing an appropriate amount into your palm and gently pressing onto your face.

PURPOSE

Moisturizing.

WARNINGS

For external use only.

Stop use and ask a doctor if rash occurs.

Do not use on damaged or broken skin.

When using this product keep out of eyes. Rinse with water to remove.

Keep out of reach of children. If swallowed, get medical help or contact a Poison Control Center right away.

DOSAGE AND ADMINISTRATION

Apply an appropriate amount to palm and gently press onto face before bedtime.